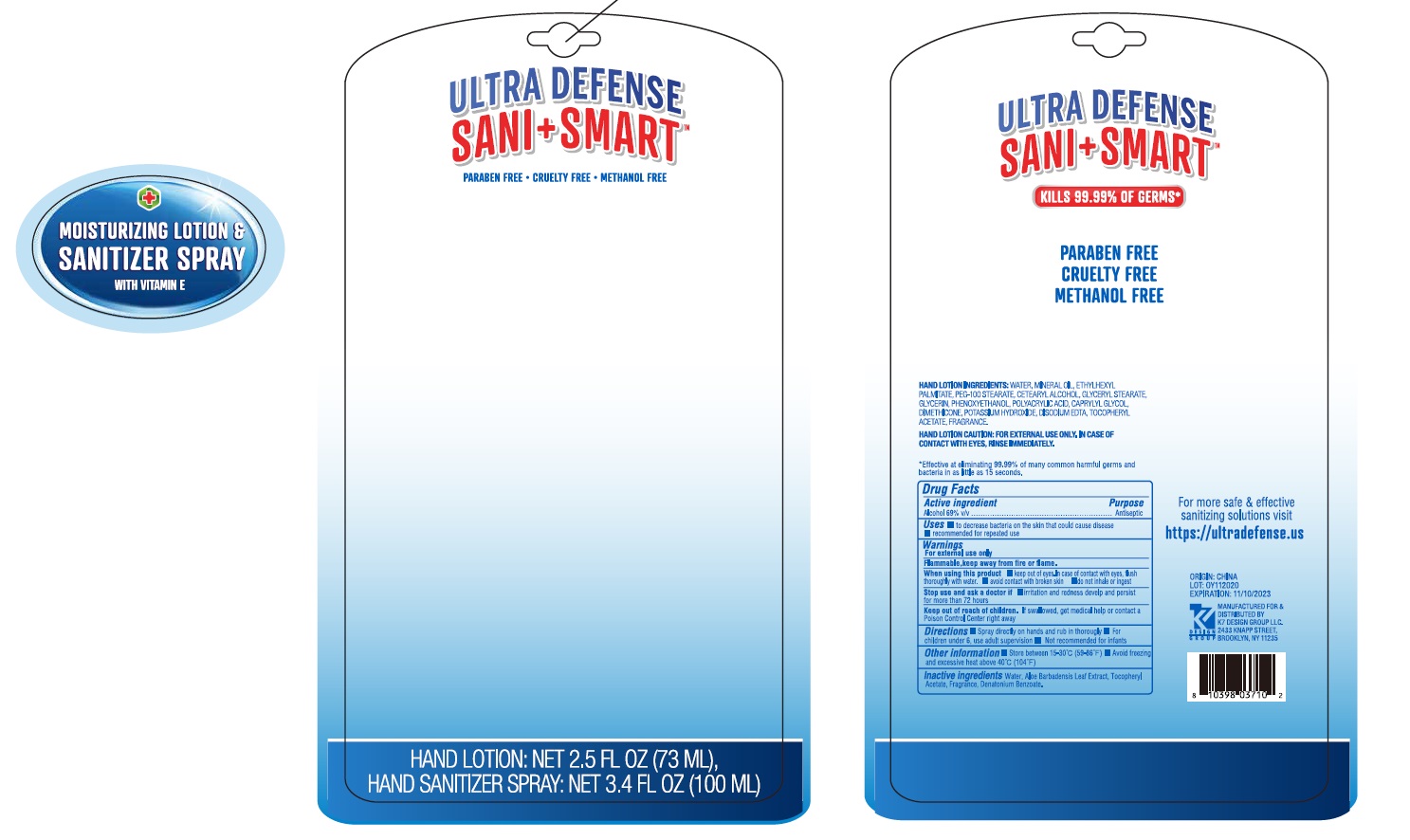 DRUG LABEL: Ultra Defense Sani Smart Moisturizing and Sanitizer
NDC: 74177-955 | Form: KIT | Route: TOPICAL
Manufacturer: K7 Design Group Inc.
Category: otc | Type: HUMAN OTC DRUG LABEL
Date: 20201029

ACTIVE INGREDIENTS: ALCOHOL 69 mL/100 mL
INACTIVE INGREDIENTS: .ALPHA.-TOCOPHEROL ACETATE; DENATONIUM BENZOATE; WATER; ALOE VERA LEAF

Ultra Defense Sani Smart Moisturizing Lotion & Sanitizer Spray

Active ingredient

Alcohol 69% v/v

Purpose

Antiseptic

Uses

- to decrease bacteria on the skin that could cause disease
- recommended for repeated use

Warnings

For external use only

Flammable, keep away from fire or flame.

When using this product

- keep out of eyes. In case of contact with eyes, flush thoroughly with water
- avoid contact with broken skin
- do not inhale or ingest

Stop use and ask a doctor if

- irritation and redness develop and persist for more than 72 hours

Keep out of reach of children.

If swallowed, get medical help or contact a Poison Control Center right away

Directions

- Spray directly on hands and rub in thoroughly
- For children under 6, use adult supervision
- Not recommended for infants

Other information

- Store between 15-30 C (59-86F)
- Avoid freezing and excessive heat above 40C (104F)

Inactive ingredients

Water, Aloe Barbadensis Leaf Extract, Tocopheryl Acetate, Fragrance, Denatonium Benzoate.

Company Information

MANUFACTURED FOR & DISTRIBUTED BY K7 DESIGN GROUP LLC. 2433 KNAPP STREET, BROOKLYN, NY 11235

ORIGIN: CHINA